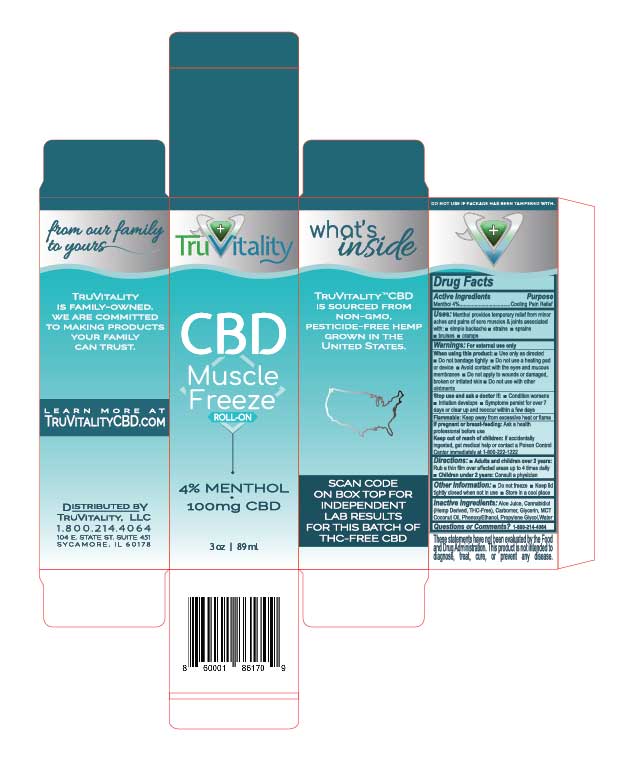 DRUG LABEL: TruVitality CBD Muscle Freeze 4% Menthol
NDC: 73155-004 | Form: GEL
Manufacturer: TRUVITALITY, LLC
Category: otc | Type: HUMAN OTC DRUG LABEL
Date: 20191231

ACTIVE INGREDIENTS: MENTHOL, UNSPECIFIED FORM 4 g/100 g
INACTIVE INGREDIENTS: MEDIUM-CHAIN TRIGLYCERIDES; PHENOXYETHANOL; PROPYLENE GLYCOL; ALOE; GLYCERIN; WATER; CARBOXYPOLYMETHYLENE; CANNABIS SATIVA SUBSP. SATIVA WHOLE

TruVitality CBD Muscle Freeze Roll-On

ACTIVE INGREDIENT

Menthol 4%.

DOSAGE AND ADMINISTRATION

Adults and children over 2 years: Rub a thin film over affected areas up to 4 times daily. Children under 2 years: Consult a physician.

Warnings: For external use only.

When using this product: Use only as directed. Do not bandage tightly. Do not use a heating pad or device. Avoid contact with the eyes and mucous membranes. Do not apply to wounds or damaged, broken or irritated skin. Do not use with other ointments.

Flammable: Keep away from excessive heat or flame.

These statements have not been evaluated by the Food and Drug Administration. This product is not intended to diagnose, treat, cure, or prevent any disease.

INACTIVE INGREDIENT

Aloe Juice, Cannabidiol (Hemp Derived, THC-Free), Carbomer, Glycerin, MCT Coconut Oil, PhenoxyEthanol, Propylene Glycol, Water.

INDICATIONS AND USAGE

Uses: Menthol provides temporary relief from minor aches and pains of sore muscles & joints associated with: simple backache, strains, sprains, bruises, cramps.

Keep out of reach of children. If accidentally ingested, get medical help or contact a Poison Control Center immediately at 1-800-222-1222.

PURPOSE

Menthol 4%: Cooling Pain Relief.

Stop use and ask a doctor if: Condition worsens, irritation develops, symptoms persist for over 7 days or clear up and reoccur within a few days.

PREGNANCY OR BREAST FEEDING

If pregnant or breast-feeding: Ask a health professional before use.

STORAGE AND HANDLING

Do not freeze. Keep lid tightly closed when not in use. Store in a cool place.

Questions or Comments?: 1-800-214-4064.